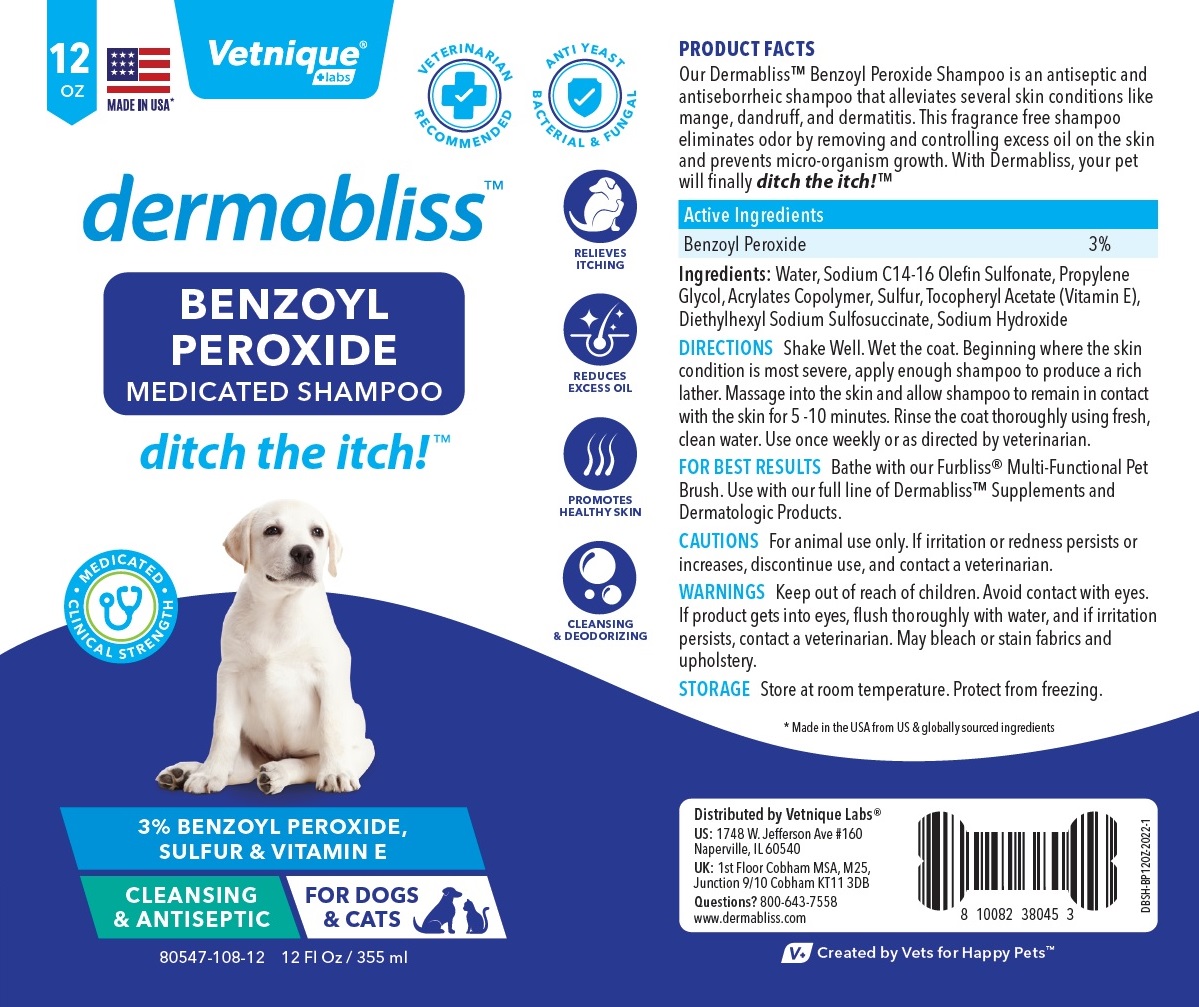 DRUG LABEL: Dermabliss
NDC: 80547-108 | Form: SHAMPOO
Manufacturer: Vetnique Labs Llc
Category: animal | Type: OTC ANIMAL DRUG LABEL
Date: 20220216

ACTIVE INGREDIENTS: BENZOYL PEROXIDE 30 mg/1 mL
INACTIVE INGREDIENTS: WATER; SODIUM C14-16 OLEFIN SULFONATE; PROPYLENE GLYCOL; SULFUR; .ALPHA.-TOCOPHEROL ACETATE; DOCUSATE SODIUM; SODIUM HYDROXIDE

dermabliss™ BENZOYL PEROXIDE MEDICATED SHAMPOO

Active Ingredients

Benzoyl Peroxide 3%

PURPOSE

Antiseptic and Antiseborrheic

INDICATIONS AND USAGE

Our Dermabliss™ Benzoyl Peroxide Shampoo is an antiseptic and antiseborrheic shampoo that alleviates several skin conditions like mange, dandruff, and dermatitis. This fragrance free shampoo eliminates odor by removing and controlling excess oil on the skin and prevents micro-organism growth. With Dermabliss, your pet will finally ditch the itch!™

DOSAGE AND ADMINISTRATION

DIRECTIONS Shake Well. Wet the coat. Beginning where the skin condition is most severe, apply enough shampoo to produce a rich lather. Massage into the skin and allow shampoo to remain in contact with the skin for 5 -10 minutes. Rinse the coat thoroughly using fresh, clean water. Use once weekly or as directed by veterinarian.

FOR BEST RESULTS Bathe with our Furbliss® Multi-Functional Pet Brush. Use with our full line of Dermabliss™ Supplements and Dermatologic Products.

PRECAUTIONS

CAUTIONS For animal use only. If irritation or redness persists or increases, discontinue use, and contact a veterinarian.

WARNINGS

WARNINGS Keep out of reach of children. Avoid contact with eyes. If product gets into eyes, flush thoroughly with water, and if irritation persists, contact a veterinarian. May bleach or stain fabrics and upholstery.

STORAGE Store at room temperature. Protect from freezing.

INACTIVE INGREDIENT

Ingredients: Water, Sodium C14-16 Olefin Sulfonate, Propylene Glycol, Acrylates Copolymer, Sulfur, Tocopheryl Acetate (Vitamin E), Diethylhexyl Sodium Sulfosuccinate, Sodium Hydroxide

MADE IN USA*

VETERINARIAN RECOMMENDED

ANTI YEAST BACTERIAL & FUNGAL

MEDICATED SHAMPOO

ditch the itch!™

MEDICATED CLINICAL STRENGTH

CLEANSING & ANTISEPTIC

FOR DOGS & CATS

RELIEVES ITCHING

REDUCES EXCESS OIL

PROMOTES HEALTHY SKIN

CLEANSING & DEODORIZING

* Made in the USA from US & globally sourced ingredients

Distributed by Vetnique Labs®
US: 1748 W. Jefferson Ave #160
Naperville, IL 60540
UK: 1st Floor Cobham MSA, M25,
Junction 9/10 Cobham KT11 3DB
Questions? 800-643-7558
www.dermabliss.com

V+ Created by Vets for Happy Pets™